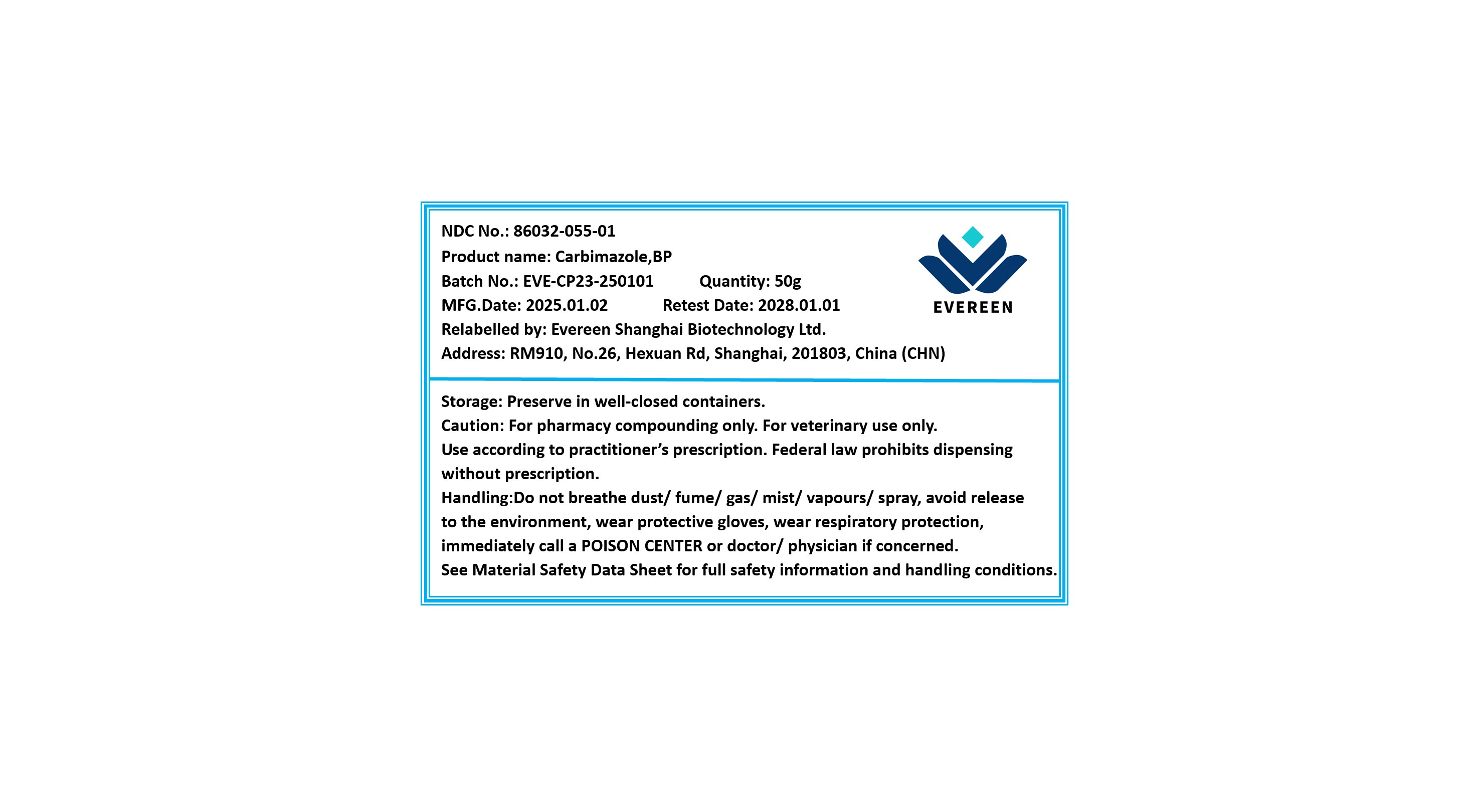 DRUG LABEL: Carbimazole
NDC: 86032-055 | Form: POWDER
Manufacturer: Evereen Shanghai Biotechnology Ltd.
Category: other | Type: BULK INGREDIENT - ANIMAL DRUG
Date: 20250728

ACTIVE INGREDIENTS: CARBIMAZOLE 1 g/1 g

Carbimazole